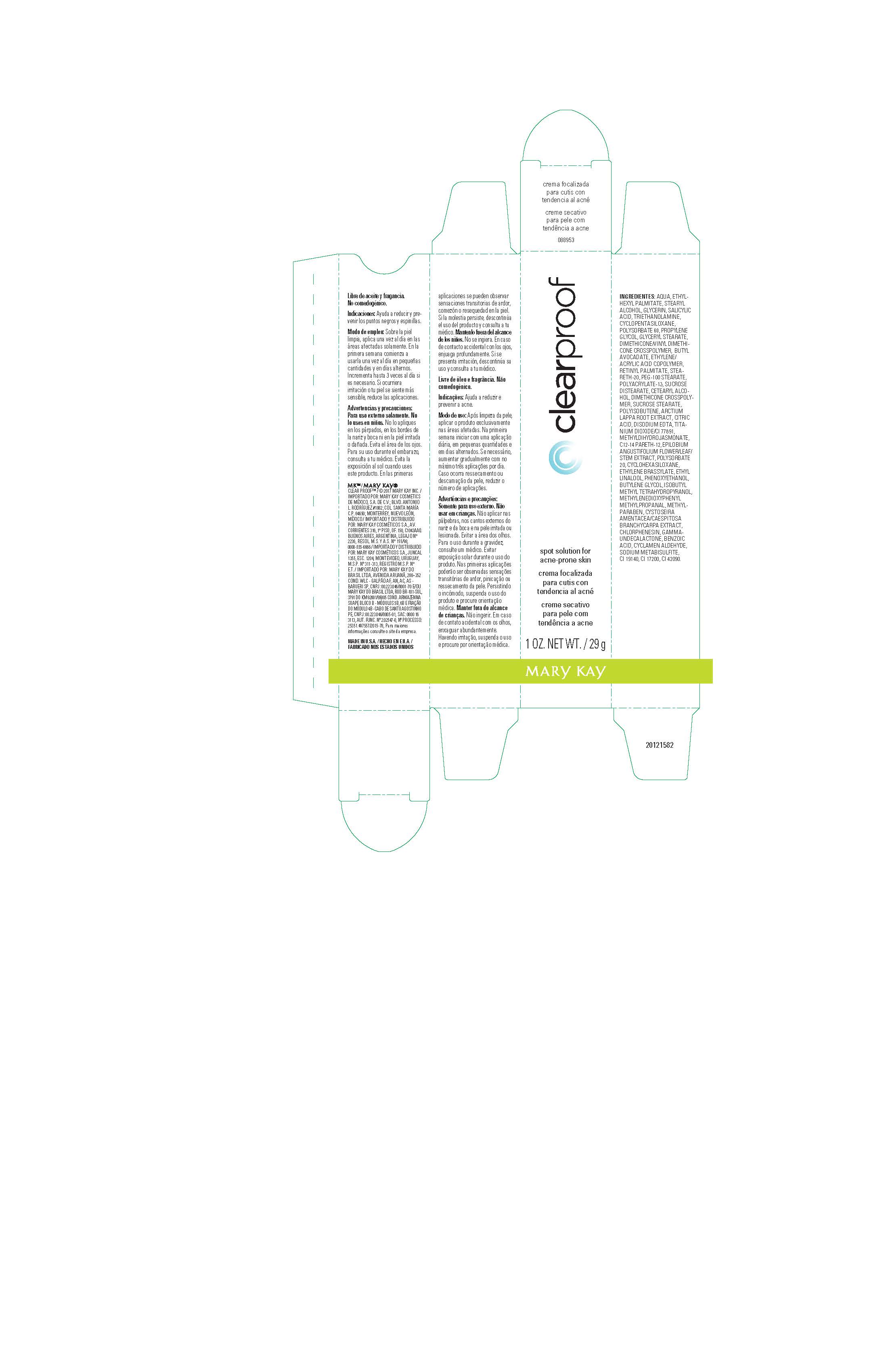 DRUG LABEL: ClearProof Spot Solution for Acne-Prone Skin
NDC: 51531-8953 | Form: CREAM
Manufacturer: Mary Kay Inc.
Category: otc | Type: HUMAN OTC DRUG LABEL
Date: 20201208

ACTIVE INGREDIENTS: SALICYLIC ACID 2 g/100 g
INACTIVE INGREDIENTS: PROPYLENE GLYCOL; SUCROSE STEARATE; BUTYL AVOCADATE; POLYSORBATE 20; VITAMIN A PALMITATE; STEARETH-20; .GAMMA.-UNDECALACTONE; GLYCERIN; PEG-100 STEARATE; CETOSTEARYL ALCOHOL; DIMETHICONE CROSSPOLYMER (450000 MPA.S AT 12% IN CYCLOPENTASILOXANE); ARCTIUM LAPPA ROOT; ETHYLENE BRASSYLATE; ETHYLHEXYL PALMITATE; TROLAMINE; POLYSORBATE 60; GLYCERYL MONOSTEARATE; DIMETHICONE/VINYL DIMETHICONE CROSSPOLYMER (SOFT PARTICLE); CITRIC ACID MONOHYDRATE; TITANIUM DIOXIDE; METHYL DIHYDROJASMONATE (SYNTHETIC); EPILOBIUM ANGUSTIFOLIUM FLOWERING TOP; CYCLOMETHICONE 6; ETHYL LINALOOL; BUTYLENE GLYCOL; 3-(3,4-METHYLENEDIOXYPHENYL)-2-METHYLPROPANAL; METHYLPARABEN; CHLORPHENESIN; BENZOIC ACID; CYCLAMEN ALDEHYDE; D&C RED NO. 33; WATER; STEARYL ALCOHOL; CYCLOMETHICONE 5; SUCROSE DISTEARATE; POLYISOBUTYLENE (2300 MW); ACRYLIC ACID/ETHYLENE COPOLYMER (600 MPA.S); C12-14 PARETH-12; PHENOXYETHANOL; EDETATE DISODIUM; 2-ISOBUTYL-4-METHYLTETRAHYDROPYRAN-4-OL; SODIUM METABISULFITE; PROPYL GALLATE; FD&C BLUE NO. 1; FD&C YELLOW NO. 5

ClearProof Spot Solution for Acne-Prone Skin LATAM

PURPOSE

Helps reduce and prevent blackheads and pimples.

Directions:

On clean skin, apply once a day only to affected areas.

In the first week, use a small amount once a day on alternate days.

Increase to up to 3 times a day if necessary.

If irritation occurs or your skin feels more sensitive, reduce applications.

Warnings:

For external use only.

Not to be used on children.

Do not apply to the eyelids, the edges of the nose and mouth, or to irritated or damaged slin.

Avoid the eye area.

For use during pregnancy, consult your doctor.

Avoid sun exposure when using this product.

In the first applications, you may experience a transient burning sensation or itchy or dry skin.

If the discomfort persists, discontinue use of the product and consult your doctor.

Keep out of the reach of children. Do not ingest

In case of accidental contact with the eyes, rinse thoroughly with water.

If irritation develops, discontinue use and consult your doctor.

INGREDIENTS:

AQUA, ETHYLHEXYL PALMITATE, STEARYL ALCOHOL, GLYCERIN, SALICYLIC ACID, TRIETHANOLAMINE,
CYCLOPENTASILOXANE, POLYSORBATE 60, PROPYLENE GLYCOL, GLYCERYL STEARATE,
DIMETHICONE/VINYL DIMETHICONE CROSSPOLYMER, BUTYL AVOCADATE, ETHYLENE/ACRYLIC ACID COPOLYMER, RETINYL PALMITATE, STEARETH-20, PEG-100 STEARATE, POLYACRYLATE-13, SUCROSE DISTEARATE, CETEARYL ALCOHOL, DIMETHICONE CROSSPOLYMER, SUCROSE STEARATE, POLYISOBUTENE, ARCTIUM LAPPA
ROOT EXTRACT, CITRIC ACID, DISODIUM EDTA, TITANIUM DIOXIDE/CI 77891, METHYLDIHYDROJASMONATE, C12-14
PARETH-12, EPILOBIUM ANGUSTIFOLIUM FLOWER/ LEAF/STEM EXTRACT, POLYSORBATE 20, CYCLOHEXASILOXANE, ETHYLENE BRASSYLATE, ETHYL LINALOOL, PHENOXYETHANOL, BUTYLENE GLYCOL, ISOBUTYL METHYL
TETRAHYDROPYRANOL, METHYLENEDIOXYPHENYL METHYLPROPANAL, METHYLPARABEN, CYSTOSEIRA
AMENTACEA/CAESPITOSA/BRANCHYCARPA EXTRACT, CHLORPHENESIN, GAMMA-UNDECALACTONE, BENZOIC
ACID, CYCLAMEN ALDEHYDE, SODIUM METABISULFITE, PROPYL GALLATE, CI 19140, CI 17200, CI 42090

Principal Display Panel - 29 g carton

clearproof

spot solution for acne-prone skin

29 g